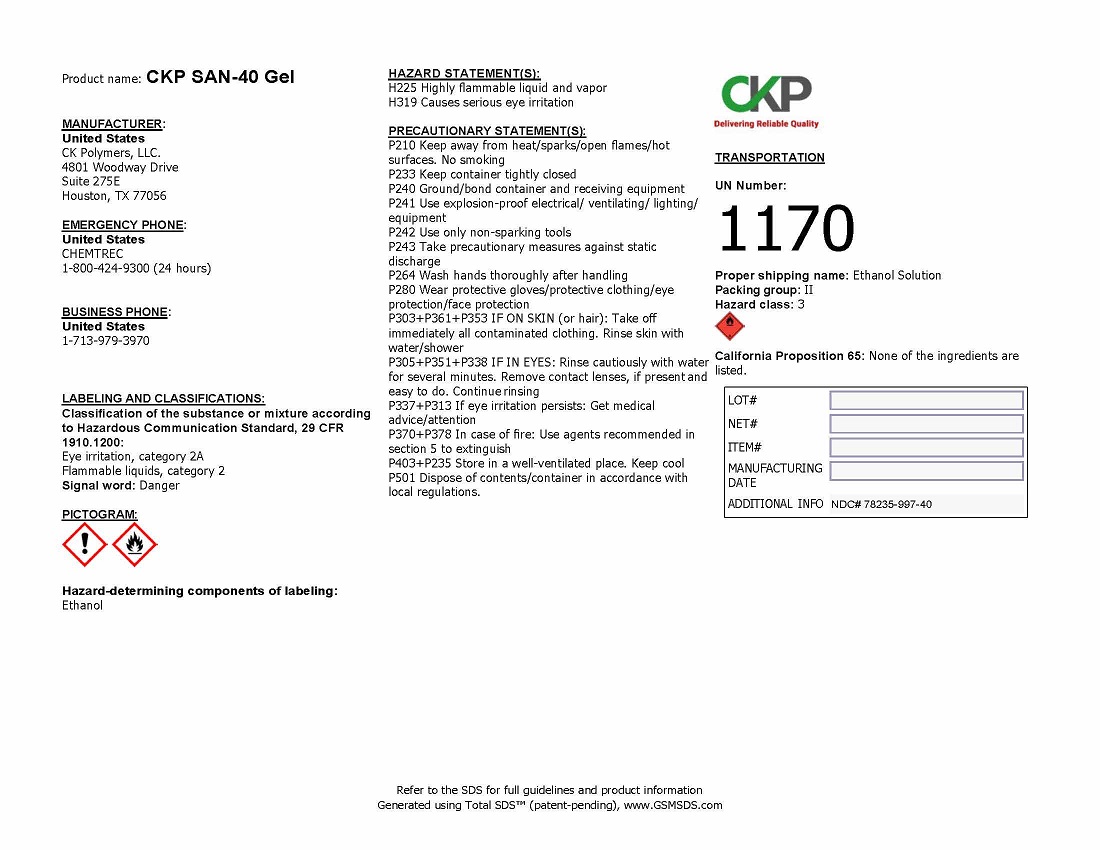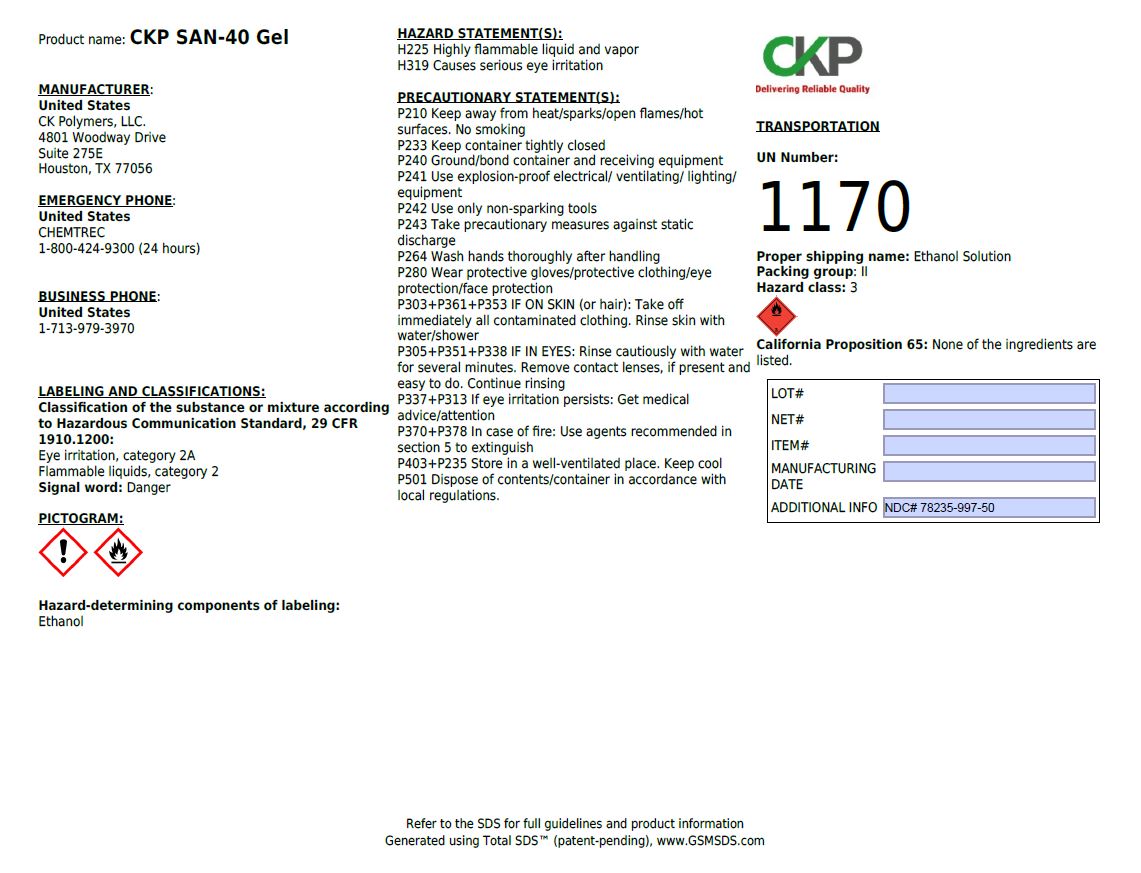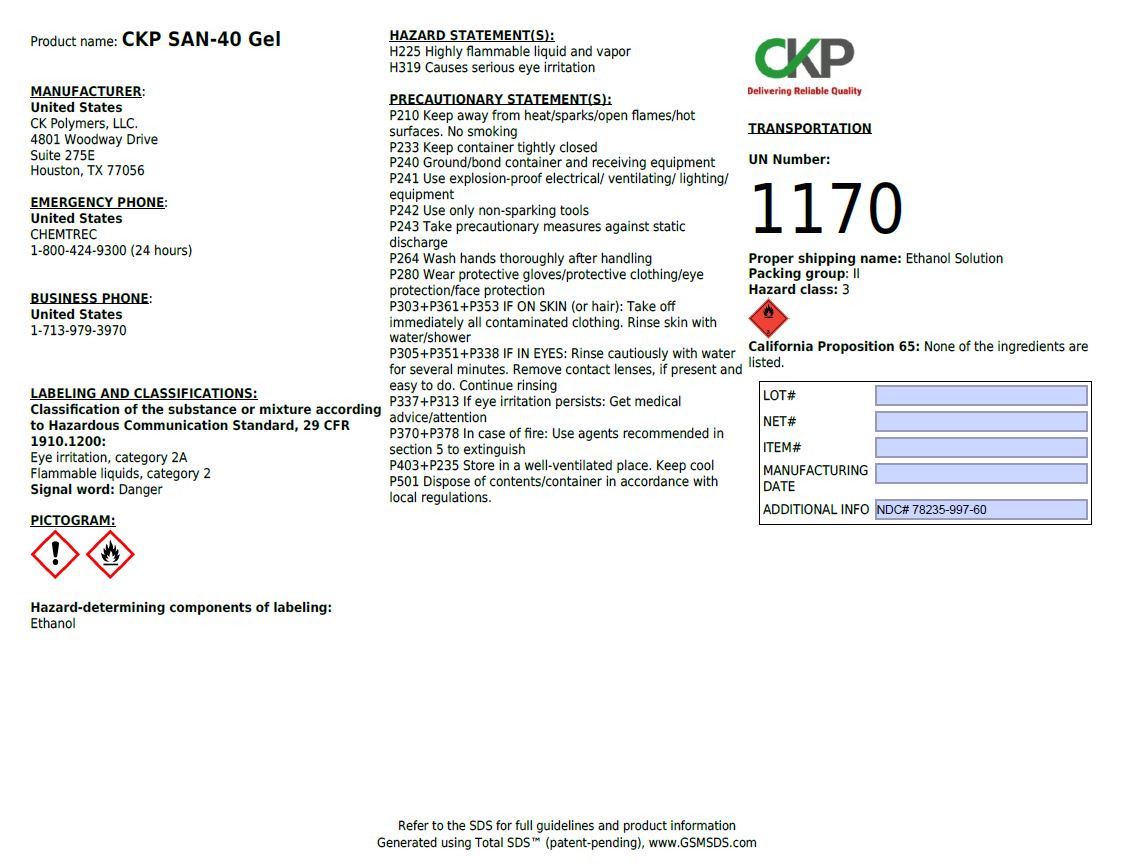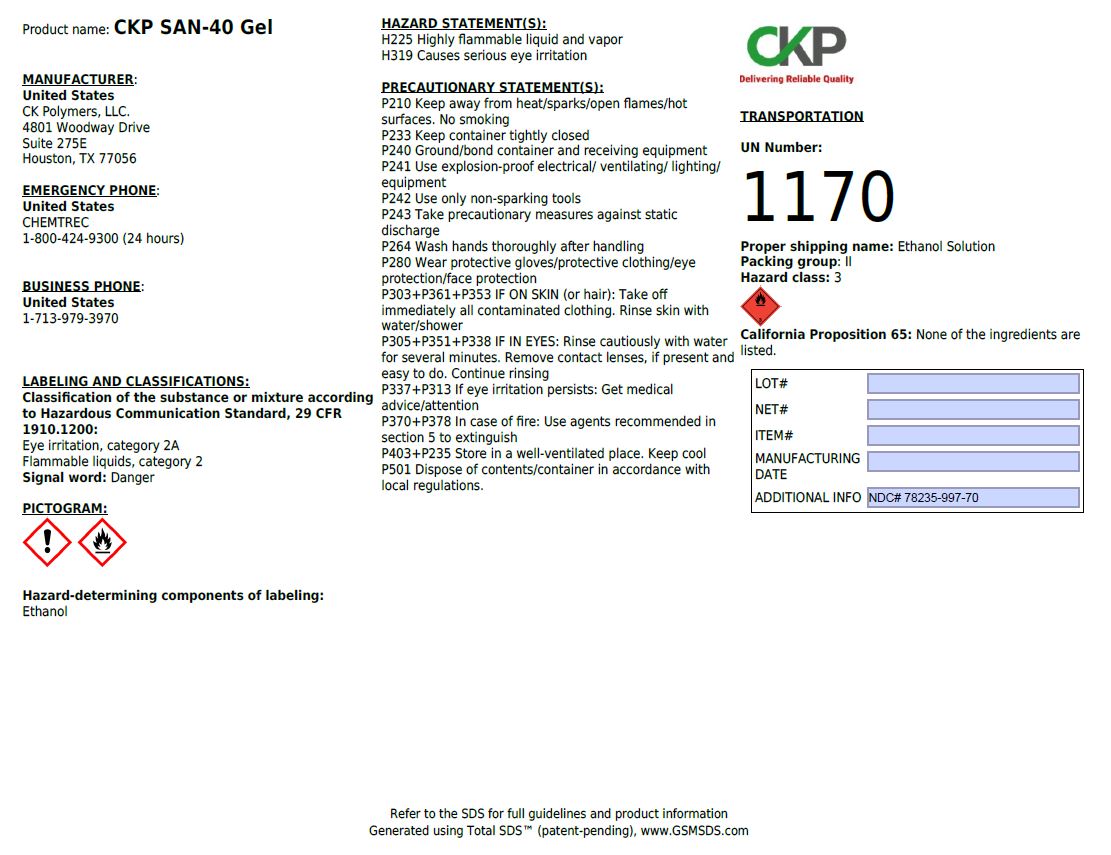 DRUG LABEL: CKP SAN-40 Gel
NDC: 78235-997 | Form: GEL
Manufacturer: CK Polymers
Category: otc | Type: HUMAN OTC DRUG LABEL
Date: 20200625

ACTIVE INGREDIENTS: ALCOHOL 1 L/1 L
INACTIVE INGREDIENTS: WATER

PACKAGE LABEL

CKP SAN-40 Gel

NDC 78235-997-40

MANUFACTURER:

United States

CK Polymers, LLC

4801 Woodway Drive

Suite 275E

Houston, TX 77056

EMERGENCY PHONE:

United States

CHEMTREC

1-800-424-9300 (24 hours)

BUSINESS PHONE:

United States

1-713-979-3970

LABELING AND CLASSIFICATIONS:

Classification of the substance or mixture according to Hazardous Communication Standard, 29 CFR 1910.1200:

Eye irritation, category 2A

Flammable liquids, category 2

Signal word: Danger

Hazard-determining components of labeling:

Ethanol

HAZARD STATEMENTS:

H224 Highly flammable liquid and vapor

H319 Causes serious eye irritation

PRECAUTIONARY STATEMENTS:

P210 Keep away from heat/sparks/open flames/hot surfaces. No smoking

P233 Keep container tightly closed

P240 Ground/bond container and receiving equipment

P241 Use explosion-proof electrical/ventilating/lighting/equipment

P242 Use only non-sparking tools

P243 Take precautionary measures against static discharge

P264 Wash hands thoroughly after handling

P280 Wear protective gloves/protective clothing/eye protection/face protection

P303+P361+P353 IF ON SKIN (or hair): Take off immediately all contaminated clothing. Rinse skin with water/shower.

P305+P351+P338 IF IN EYES: Rinse cautiously with water for several minutes. Remove contact lenses, if present and easy to do. Continue rinsing

P337+P313 If eye irritation persists: Get medical advice/attention

P370+P378 In case of fire: Use agents recommended in section 5 to extinguish

P403+P235 Store in a well-ventilated place. Keep cool

P501 Dispose of contents/container in accordance with local regulations.

TRANSPORTATION:

UN Number: 1170

Proper shipping name: Ethanol Solution

Packing group: II

Hazard class: 3

California Proposition 65: None of the ingredients are listed.

Refer to the SDS for full guidelines and product information

NDC 78235-997-50

NDC 78235-997-60

NDC 78235-997-70